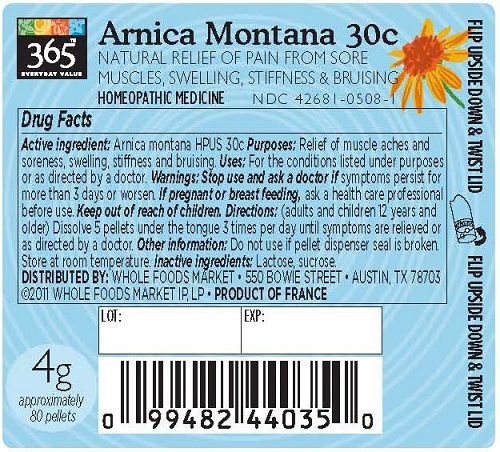 DRUG LABEL: Arnica Montana
NDC: 42681-0508 | Form: PELLET
Manufacturer: Whole Foods Market
Category: homeopathic | Type: HUMAN OTC DRUG LABEL
Date: 20160708

ACTIVE INGREDIENTS: ARNICA MONTANA 30 [hp_C]/1 1
INACTIVE INGREDIENTS: lactose; sucrose

Arnica Montana 30c

Active Ingredient: Arnica Montana HPUS 30c

DOSAGE AND ADMINISTRATION

Directions: (adults and children 12 years and older) Dissolve 5 pellets under the tongue 3 times per day until symptoms are relieved or as directed by a doctor.

USES

For the conditions listed under purposes or as directed by a doctor.

WARNINGS

Warnings: Stop use and ask a doctor if symptoms persist for more than 3 days or worsen.

PREGNANCY OR BREAST FEEDING

If pregnant or breast-feeding, ask a health care professional before use.

Keep out of reach of children.

OTHER SAFETY INFORMATION

Store at room temperature.

other information: Do not use if pellet dispenser seal is broken.

Inactive Ingredients: Lactose, sucrose.

PURPOSE

Purposes: relief of muscle aches and soreness, swelling, stiffness and bruising.